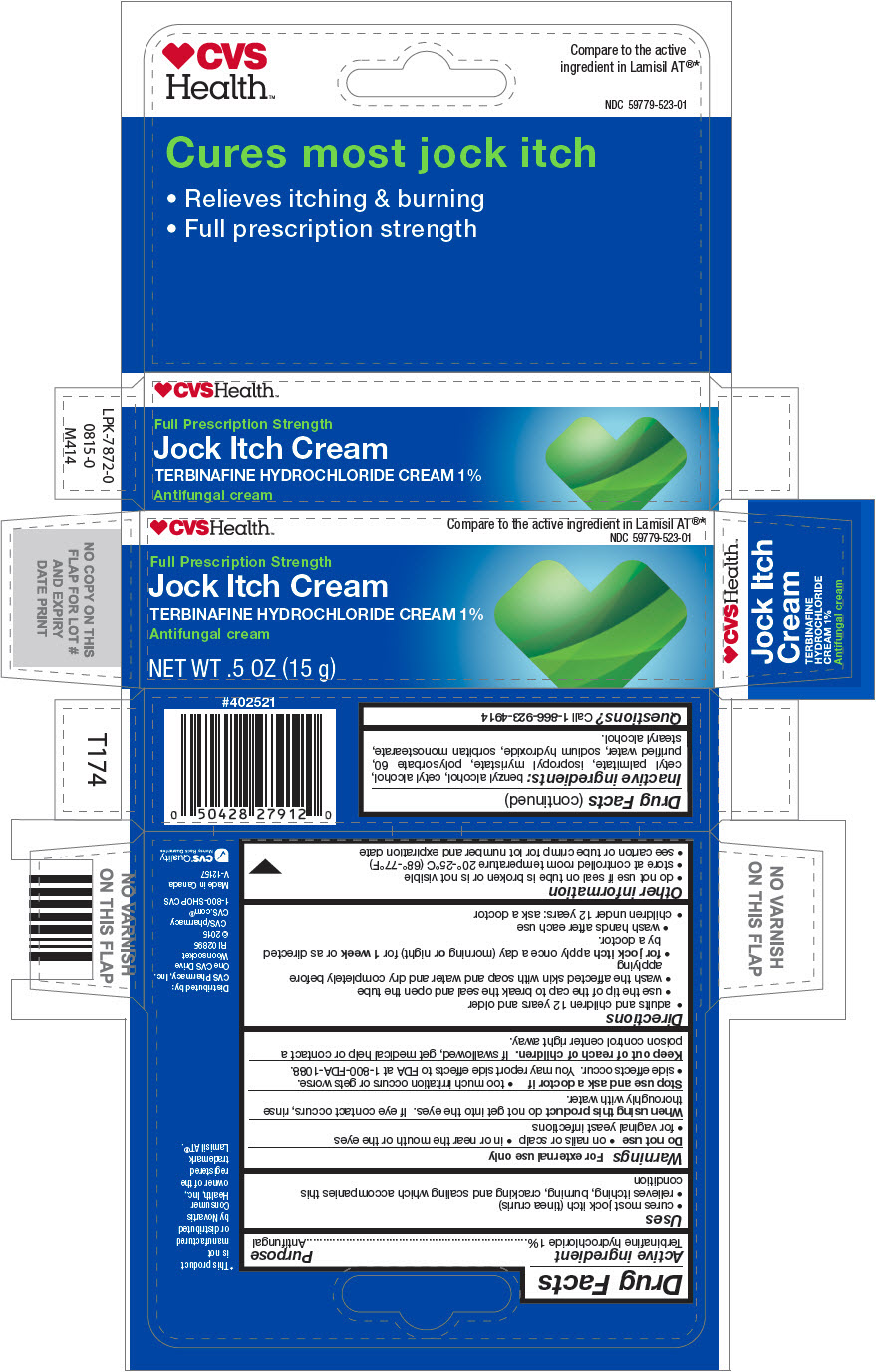 DRUG LABEL: CVS
NDC: 59779-523 | Form: CREAM
Manufacturer: CVS Pharmacy
Category: otc | Type: HUMAN OTC DRUG LABEL
Date: 20251125

ACTIVE INGREDIENTS: TERBINAFINE HYDROCHLORIDE 1 g/100 g
INACTIVE INGREDIENTS: BENZYL ALCOHOL; CETYL ALCOHOL; CETYL PALMITATE; ISOPROPYL MYRISTATE; POLYSORBATE 60; WATER; SODIUM HYDROXIDE; SORBITAN MONOSTEARATE; STEARYL ALCOHOL

CVS

Drug Facts

Active ingredient

Terbinafine hydrochloride 1%

Purpose

Antifungal

Uses

- cures most jock itch (tinea cruris)
- relieves itching, burning, cracking and scaling which accompanies this condition

Warnings

For external use only

Do not use

- on nails or scalp
- in or near the mouth or the eyes
- for vaginal yeast infections

WHEN USING

When using this productdo not get into the eyes. If eye contact occurs, rinse thoroughly with water.

Stop use and ask a doctor if

- too much irritation occurs or gets worse.
- side effects occur. You may report side effects to FDA at 1-800-FDA-1088.

Keep out of reach of children.If swallowed, get medical help or contact a poison control center right away.

Directions

- adults and children 12 years and older
  - use the tip of the cap to break the seal and open the tube
  - wash the affected skin with soap and water and dry completely before applying
  - for jock itchapply once a day (morning ornight) for 1 weekor as directed by a doctor.
  - wash hands after each use
- children under 12 years: ask a doctor

Other information

- do not use if seal on tube is broken or is not visible
- store at controlled room temperature 20°-25°C (68°-77°F)
- see carton or tube crimp for lot number and expiration date

Inactive ingredients

benzyl alcohol, cetyl alcohol, cetyl palmitate, isopropyl myristate, polysorbate 60, purified water, sodium hydroxide, sorbitan monostearate, stearyl alcohol.

Questions?

Call 1-866-923-4914

Distributed by:
CVS Pharmacy, Inc.
One CVS Drive
Woonsocket
RI 02895

PRINCIPAL DISPLAY PANEL - 15 g Tube Carton

CVSHealth™

Compare to the active ingredient in Lamisil AT®*
NDC 59779-523-01

Full Prescription Strength
Jock Itch Cream
TERBINAFINE HYDROCHLORIDE CREAM 1%
Antifungal cream

NET WT .5 OZ (15 g)